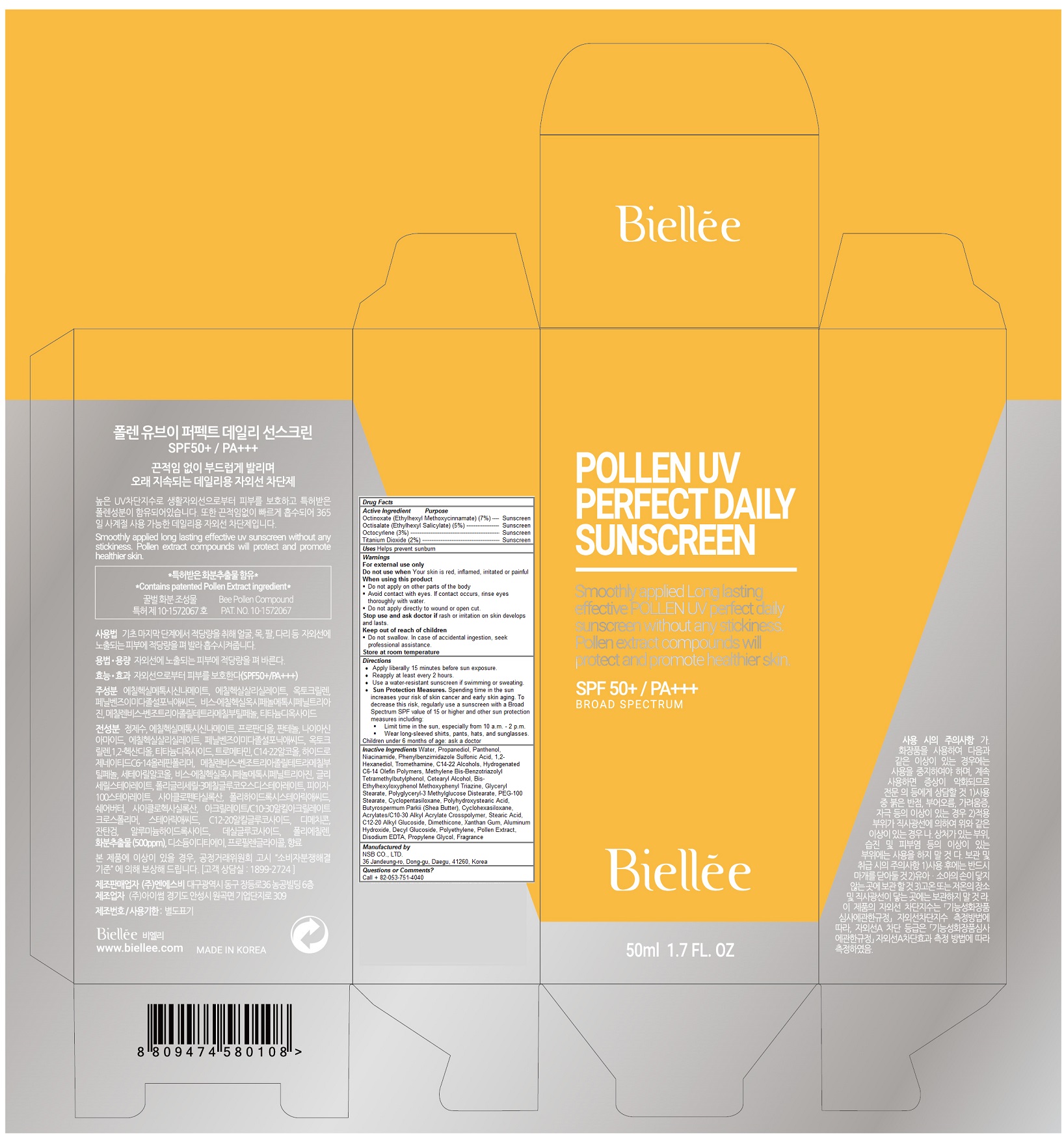 DRUG LABEL: Pollen UV Perfect Daily Sunscreen
NDC: 70784-006 | Form: CREAM
Manufacturer: NSB Co., Ltd.
Category: otc | Type: HUMAN OTC DRUG LABEL
Date: 20190107

ACTIVE INGREDIENTS: OCTINOXATE 3.5 g/50 mL; OCTISALATE 2.5 g/50 mL; OCTOCRYLENE 1.5 g/50 mL; TITANIUM DIOXIDE 1 g/50 mL
INACTIVE INGREDIENTS: WATER; PANTHENOL; NIACINAMIDE; ENSULIZOLE; 1,2-HEXANEDIOL; TROMETHAMINE; C14-22 ALCOHOLS; BISOCTRIZOLE; CETOSTEARYL ALCOHOL; BEMOTRIZINOL; GLYCERYL MONOSTEARATE; PEG-100 STEARATE; CYCLOMETHICONE 5; POLYHYDROXYSTEARIC ACID (2300 MW); SHEA BUTTER; CYCLOMETHICONE 6; CARBOMER INTERPOLYMER TYPE A (ALLYL SUCROSE CROSSLINKED); STEARIC ACID; C12-20 ALKYL GLUCOSIDE; DIMETHICONE; XANTHAN GUM; ALUMINUM HYDROXIDE; DECYL GLUCOSIDE; HIGH DENSITY POLYETHYLENE; BEE POLLEN; EDETATE DISODIUM; PROPYLENE GLYCOL

Pollen UV Perfect Daily Sunscreen

Active Ingredients

Octinoxate (Ethylhexyl Methoxycinnamate) (7%)

Octisalate (Ethylhexyl Salicylate) (5%)

Octocyrlene (3%)

Titanium Dioxide (2%)

Purpose

Sunscreen

Keep out of reach of children

Do not swallow. In case of accidental ingestion, seek professional assistance

Warnings

For external use only
Do not use when Your skin is red, inflamed, irritated or painful
When using this product
 Do not apply on other parts of the body
 Avoid contact with eyes. If contact occurs, rinse eyes thoroughly with water.
 Do not apply directly to wound or open cut.
Stop use and ask doctor if rash or irritation on skin develops and lasts.

Store at room temperature

Uses

Helps prevent sunburn

Directions

• Apply liberally 15 minutes before sun exposure.
• Reapply at least every 2 hours.
• Use a water-resistant sunscreen if swimming or sweating.
• Sun Protection Measures. Spending time in the sun increases your risk of skin cancer and early skin aging. To decrease this risk, regularly use a sunscreen with a Broad Spectrum SPF value of 15 or higher and other sun protection measures including:
 Limit time in the sun, especially from 10 a.m. - 2 p.m.
 Wear long-sleeved shirts, pants, hats, and sunglasses.
Children under 6 months of age: ask a doctor

Inactive Ingredients

Water, Propanediol, Panthenol, Niacinamide, Phenylbenzimidazole Sulfonic Acid, 1,2-Hexanediol, Tromethamine, C14-22 Alcohols, Hydrogenated C6-14 Olefin Polymers, Methylene Bis-Benzotriazolyl Tetramethylbutylphenol, Cetearyl Alcohol, Bis-Ethylhexyloxyphenol Methoxyphenyl Triazine, Glyceryl Stearate, Polyglyceryl-3 Methylglucose Distearate, PEG-100 Stearate, Cyclopentasiloxane, Polyhydroxystearic Acid, Butyrospermum Parkii (Shea Butter), Cyclohexasiloxane, Acrylates/C10-30 Alkyl Acrylate Crosspolymer, Stearic Acid, C12-20 Alkyl Glucoside, Dimethicone, Xanthan Gum, Aluminum Hydroxide, Decyl Glucoside, Polyethylene, Pollen Extract, Disodium EDTA, Propylene Glycol, Fragrance